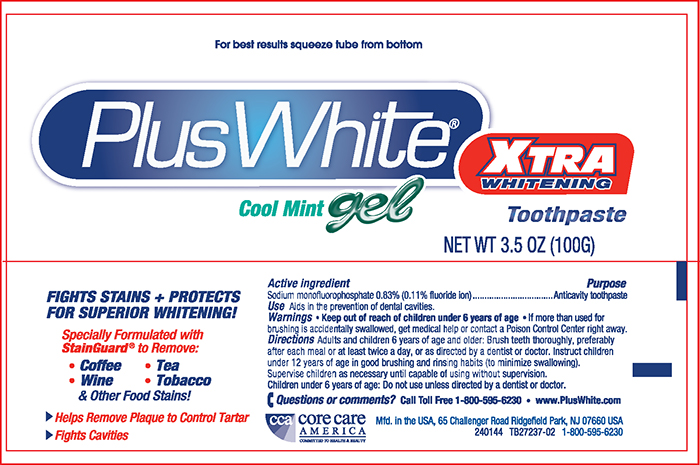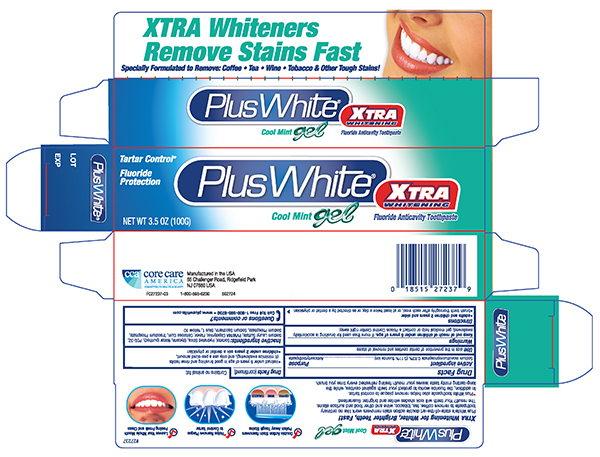 DRUG LABEL: Plus White Extra Whitening
NDC: 61543-1606 | Form: GEL, DENTIFRICE
Manufacturer: CCA Industries, Inc.
Category: otc | Type: HUMAN OTC DRUG LABEL
Date: 20191226

ACTIVE INGREDIENTS: SODIUM MONOFLUOROPHOSPHATE 0.83 g/100 g
INACTIVE INGREDIENTS: GLYCERIN; POLYETHYLENE GLYCOL 1450; WATER; HYDRATED SILICA; COPOVIDONE K25-31; TRISODIUM DIPHOSPHATE; SODIUM LAURYL SULFATE; CARBOXYMETHYLCELLULOSE SODIUM; SACCHARIN SODIUM; SORBITOL; SODIUM PHOSPHATE, MONOBASIC

Plus White Extra Whitening Gel

Active Ingredient

Sodium Monofluorophosphate 0.83% (0.11% w/v fluoride ion)

Purpose

Anticavity Toothpaste

Uses

Aids in the prevention of dental cavitites.

Warnings

If more than used for brushing is accidentally swallowed, get medical help or contact a Poison Control Center right away.

Directions

- Adults and children 2 years and older
- Brush teeth thoroughly, after each meal, or at least twice a day, or as directed by a dentist or physician
- instruct under 6 years of age in good brushing and rinse habits (it minimizes swallowing), and only use a pea size amount.
- Children under 2 years ask a dentist or physician

INACTIVE INGREDIENT

Inactive ingredients Sorbitol, Hydrated Silica, Glycerin, Water (Purified), PEG 32, Flavor, Sodium lauryl Sulfate, PVM/MA Copolymer, Flavor, Cellulose Gum, Trisodium Phosphate, Sodium Phosphate, Sodium Saccharin, Blue 1, yellow 10

Questions or comments? Call Toll Free1-800-595-6230
- www.pluswhite.com

Principal Display Panel -Tube 3.5 oz

Plus+White
Extra Whitening Gel TOOTHPASTE
Net Wt 3.5 oz (100G) - Fluoride Anticavity Toothpaste

Principal Display Panel - Carton 3.5 oz

Plus + White

Extra Whitening Gel Toothpaste

NET WT 3.5 oz (100G) Fluoride Anticavity Toothpaste